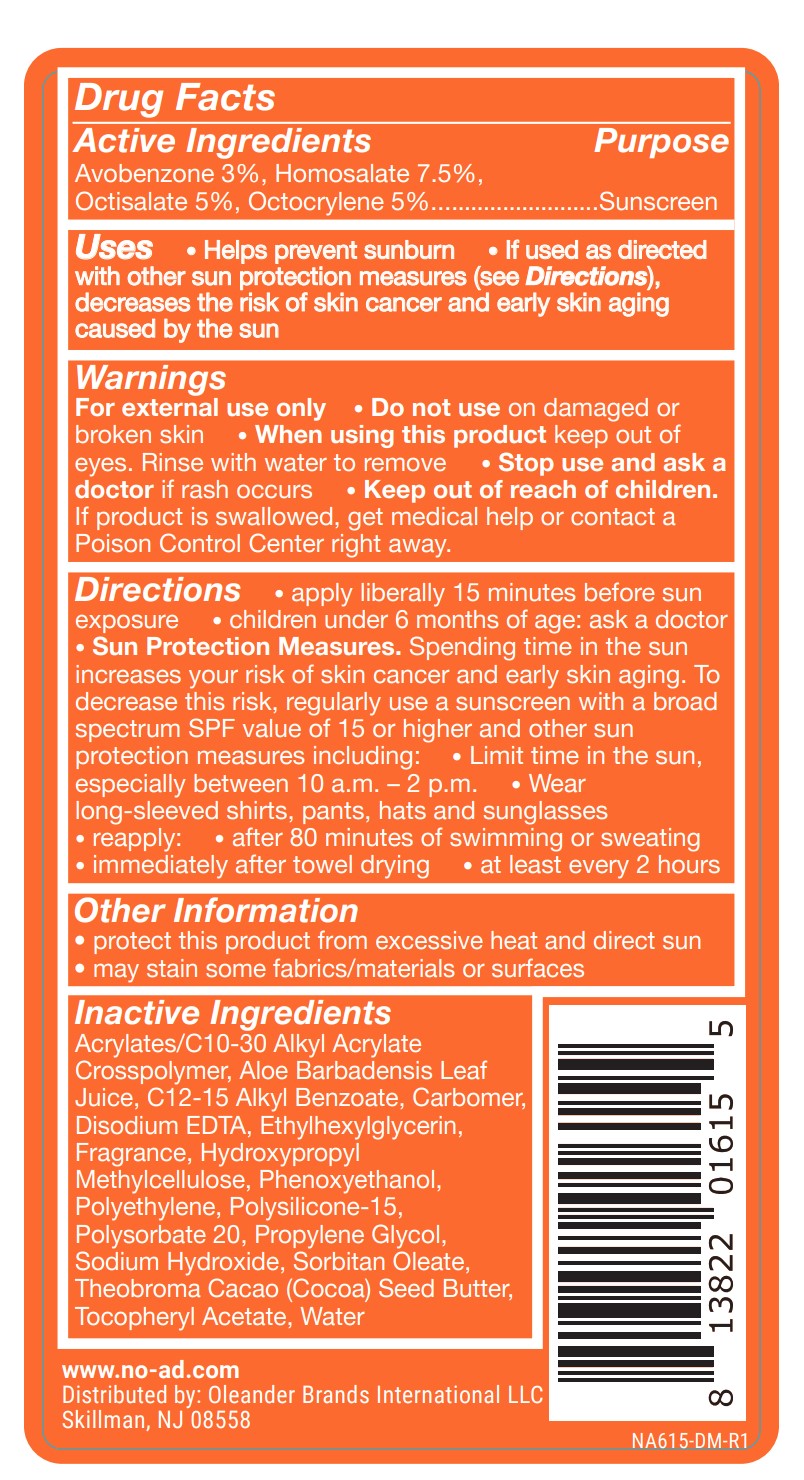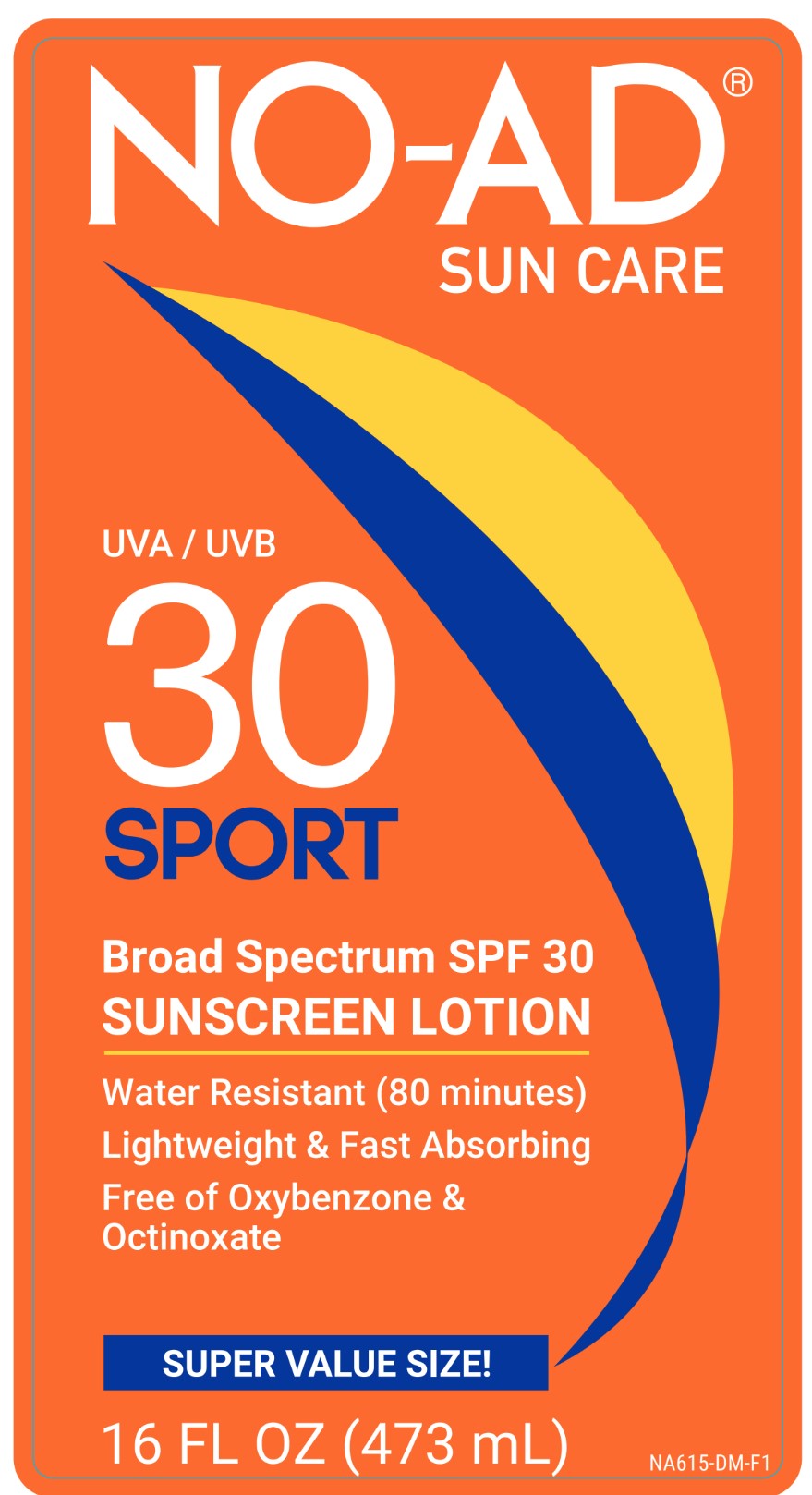 DRUG LABEL: Sun Basics
NDC: 58443-0646 | Form: LOTION
Manufacturer: Prime Enterprises Inc.
Category: otc | Type: HUMAN OTC DRUG LABEL
Date: 20240117

ACTIVE INGREDIENTS: AVOBENZONE 29.1 g/1 mL; OCTISALATE 48.5 g/1 mL; OCTOCRYLENE 48.5 g/1 mL; HOMOSALATE 72.75 g/1 mL
INACTIVE INGREDIENTS: HYPROMELLOSE, UNSPECIFIED; SORBITAN MONOOLEATE; POLYSORBATE 20; COCOA BUTTER; WATER; SODIUM HYDROXIDE; PHENOXYETHANOL; ETHYLHEXYLGLYCERIN; PROPYLENE GLYCOL; ALOE VERA LEAF; .ALPHA.-TOCOPHEROL ACETATE; EDETATE DISODIUM; HIGH DENSITY POLYETHYLENE; CARBOMER INTERPOLYMER TYPE A (ALLYL SUCROSE CROSSLINKED); ALKYL (C12-15) BENZOATE; CARBOMER 980; POLYSILICONE-15

NO-AD Broad Spectrum SPF 30 Sunscreen Lotion

Active Ingredients

Avobenzone 3%

Homosalate 7.5%

Octisalate 5%

Octocrylene 5%

Purpose

Sunscreen

Uses

• Helps prevent sunburn

• If used as directed with other sun protection measures (See Directions), decreases the risk of skin cancer and early skin aging caused by the sun.

Warnings

For external use only

Do not use on damaged or broken skin

When using this product keep out of eyes. Rinse with water to remove

Stop use and ask a doctor if rash occurs

Keep out of reach of children. If product is swallowed, get medical help or contact a Poison Control Center right away.

Directions

- apply liberally 15 minutes before sun exposure
- children under 6 months of age: ask a doctor
- Sun Protection Measures.Spending time in the sun increases your risk of skin cancer and early skin aging. To decrease this risk, regularly use a sunscreen with a broad spectrum SPF value of 15 or higher and other sun protection measures including:
- Limit time in the sun, especially from 10 a.m. – 2 p.m.
- Wear long-sleeved shirts, pants, hats, and sunglasses
- reapply:
- after 80 minutes of swimming or sweating
- immediately after towel drying
- at least every 2 hours

Other information

- protect this product from excessive heat and direct sun
- may stain some fabrics/materials or surfaces

Inactive ingredients

Acrylates/C10-30 Alkyl Acrylate Crosspolymer, Aloe Barbadensis Leaf Juice, C12-15 Alkyl Benzoate, Carbomer, Disodium EDTA, Ethylhexylglycerin, Fragrance, Hydroxypropyl Methylcellulose, Phenoxyethanol, Polyethylene, Polysilicone-15, Polysorbate 20, Propylene Glycol, Sodium Hydroxide, Sorbitan Oleate, Theobroma Cacao (Cocoa) Seed Butter, Tocopheryl Acetate, Water